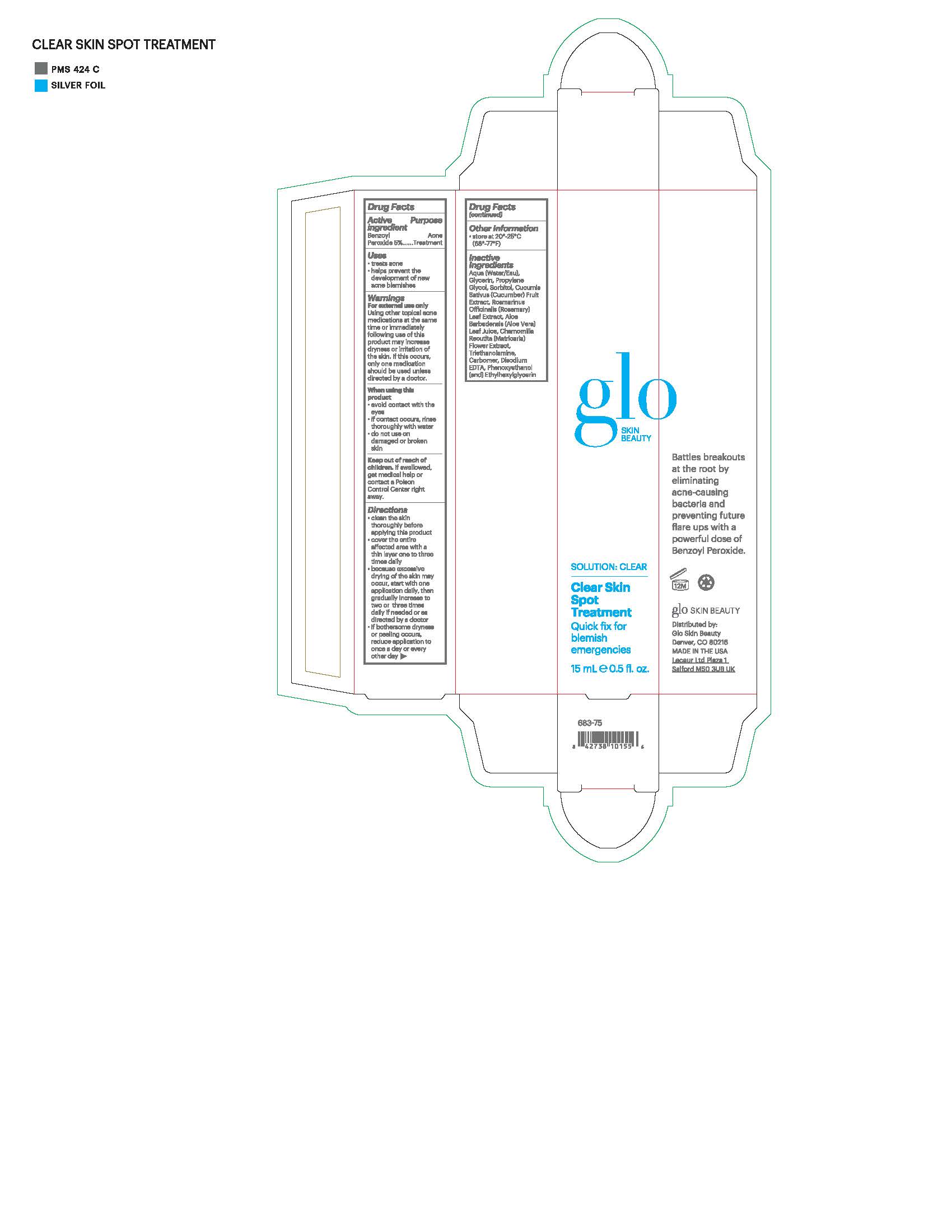 DRUG LABEL: glo SKIN BEAUTY Clear Skin Spot Treatment
NDC: 60541-1800 | Form: LIQUID
Manufacturer: Hayden Caleel LLC
Category: otc | Type: HUMAN OTC DRUG LABEL
Date: 20250105

ACTIVE INGREDIENTS: BENZOYL PEROXIDE 5 g/100 g
INACTIVE INGREDIENTS: WATER; GLYCERIN; PROPYLENE GLYCOL; SORBITOL; CUCUMIS SATIVUS WHOLE; ROSMARINUS OFFICINALIS WHOLE; ALOE VERA LEAF; MATRICARIA CHAMOMILLA; TRIETHANOLAMINE DIOLEATE; CARBOMER 940; DISODIUM EDTA-COPPER; PHENOXYETHANOL; ETHYLHEXYLGLYCERIN

DRUG FACTS

Active Ingredients

Benzoyl Peroxide 5%

Purpose

Acne Treatment

Uses

- Treats Acne
- Helps prevent the development of new acne blemishes

Warnings

Using other topical acne medications at the same tiem or immediatly following use of this prouct may increase dryness or irritation of the skin. If this occurs, only one medication shoul be used unless directed by a doctor.

For external use only
When using this product
• avoid contact with the eyes
• if contact occurs, rinse thoroughly with water
• do not use on damaged or broken skin

Keep out of reach of children. If swallowed, get medical help
or contact a Poison Control Center right away.

Directions

- Clean the skin thoroughly before applying this product
- Cover the entire affected area with a thin layer one to three times daily
- Because excessive drying of the skin may occur, start with one application daily, then gradually increase to two or three times daily if needed or as directed by a doctor
- If bothersome dryness or peeling occurs, reduce use to once a day or every other ay

Inactive Ingredients

Water, Glycerin, Propylene Glycol, Sorbitol, Cucumis Sativa (Cucumber) Fruit Extract, Rosmarinus Officinalis (Rosemary) Leaf Extract, Aloe Barbadensis (Aloe Vera) Leaf Juice, Chamomilla Recutita (Matricaria) Flower Extract, Triethanolamine, Carbomer, Disodium EDTA, Phenoxyethanol, Ethylhexylglycerin